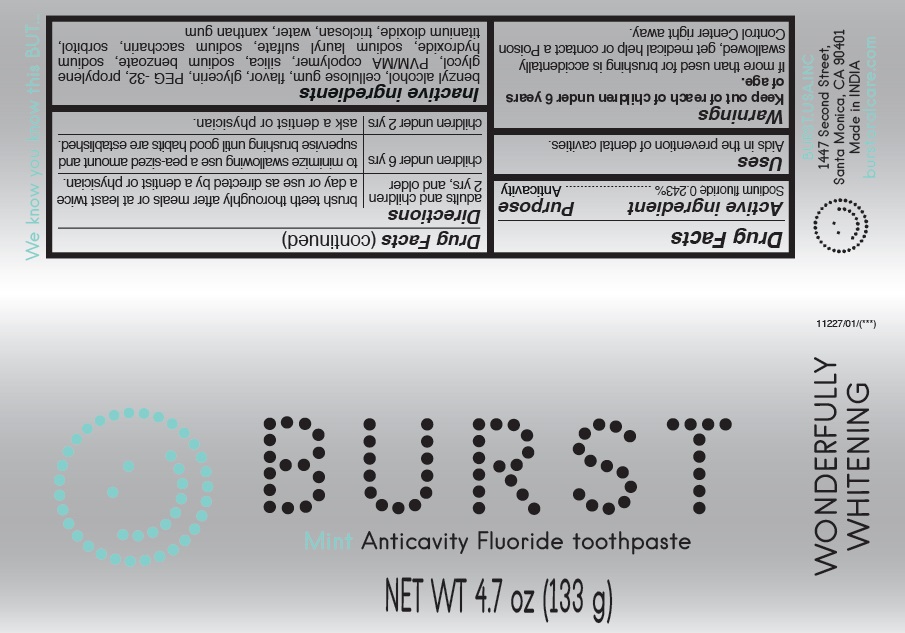 DRUG LABEL: BURST
NDC: 71275-001 | Form: PASTE, DENTIFRICE
Manufacturer: BURST.USA.Inc
Category: otc | Type: HUMAN OTC DRUG LABEL
Date: 20200122

ACTIVE INGREDIENTS: SODIUM FLUORIDE 0.243 mg/1 g
INACTIVE INGREDIENTS: BENZYL ALCOHOL; CARBOXYMETHYLCELLULOSE; GLYCERIN; POLYETHYLENE GLYCOL 1500; PROPYLENE GLYCOL; TRICLOSAN; SILICON DIOXIDE; SODIUM BENZOATE; SODIUM HYDROXIDE; SODIUM LAURYL SULFATE; SACCHARIN SODIUM; SORBITOL; XANTHAN GUM; WATER; TITANIUM DIOXIDE

Burst Toothpaste

Active Ingredient

Sodium fluoride 0.243%

Purpose

Anticavity

Uses

Aids in the prevention of dental cavities

Keep out of the reach of children

under 6 years of age.

Warnings

If more than used for brushing is accidentally swallowed, get medical help or contact a Poison Control Center right away

Directions

adults and children 2 yrs and older brush teeth thoroughly after meals or at least twice a day or use as directed by a dentist or physician. children under 6 yrs to minimize swallowing use a pea-sized amount and brushing until good habits are established. children under 2 years: ask a dentist or physician

Inactive ingredients

benzyl alcohol, cellulose gum, flavor, glycerin, PEG-32, propylene glycol, PVM/MA copolymer, silica, sodium benzoate, sodium hydroxide, sodium lauryl sulfate, sodium saccharin, sorbitol, titanium dioxide, water, xanthan gum